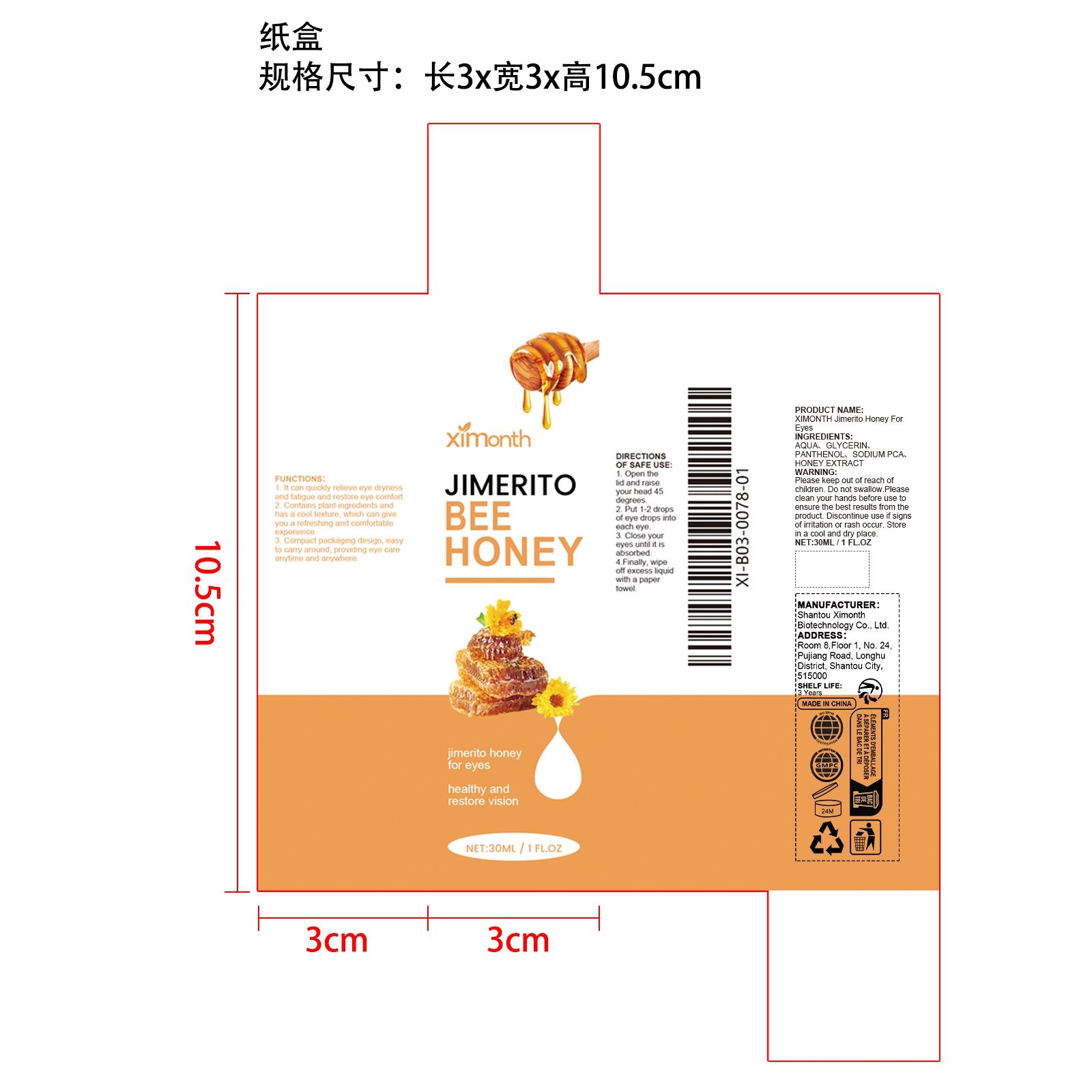 DRUG LABEL: XIMONTH Jimerito Honey For Eyes
NDC: 84989-008 | Form: LIQUID
Manufacturer: Shantou Ximonth Biotechnology Co., Ltd.
Category: otc | Type: HUMAN OTC DRUG LABEL
Date: 20251126

ACTIVE INGREDIENTS: HONEY 0.006 mg/30 mg
INACTIVE INGREDIENTS: SODIUM PCA 0.3 mg/30 mg; AQUA 28.044 mg/30 mg; PANTHENOL 0.45 mg/30 mg; GLYCERIN 1.2 mg/30 mg

ACTIVE INGREDIENT

HONEY

WHEN USING

1. Open the lid and raise your head 45 degrees.

2. Put 1-2 drops of eye drops into each eye.

3. Close your eyes until it is absorbed.

4.Finally, wipe off excess liquid with a paper towel.

PURPOSE

1. It can quickly relieve eye dryness and fatigue and restore eye comfort.

2. Contains plant ingredients and has a cool texture, which can give you a refreshing and comfortable experience.

3. Compact packaging design, easy to carry around, providing eye care anytime and anywhere.

WARNINGS

Please keep out of reach of children. Do not swallow.Please clean your hands before use to ensure the best results from the product. Discontinue use if signs of irritation or rash occur. Store in a cool and dry place.

STOP USE

Discontinue use if signs of irritation or rash occur.

DO NOT USE

Discontinue use if signs of irritation or rash occur.

KEEP OUT OF REACH OF CHILDREN

Please keep out of reach of children. Do not swallow.

STORAGE AND HANDLING

Store in a cool and dry place.

INACTIVE INGREDIENT

AQUA、GLYCERIN、PANTHENOL、SODIUM PCA

INDICATIONS AND USAGE

1. Open the lid and raise your head 45 degrees.

2. Put 1-2 drops of eye drops into each eye.

3. Close your eyes until it is absorbed.

4.Finally, wipe off excess liquid with a paper towel.

DOSAGE AND ADMINISTRATION

Put 1-2 drops of eye drops into each eye.